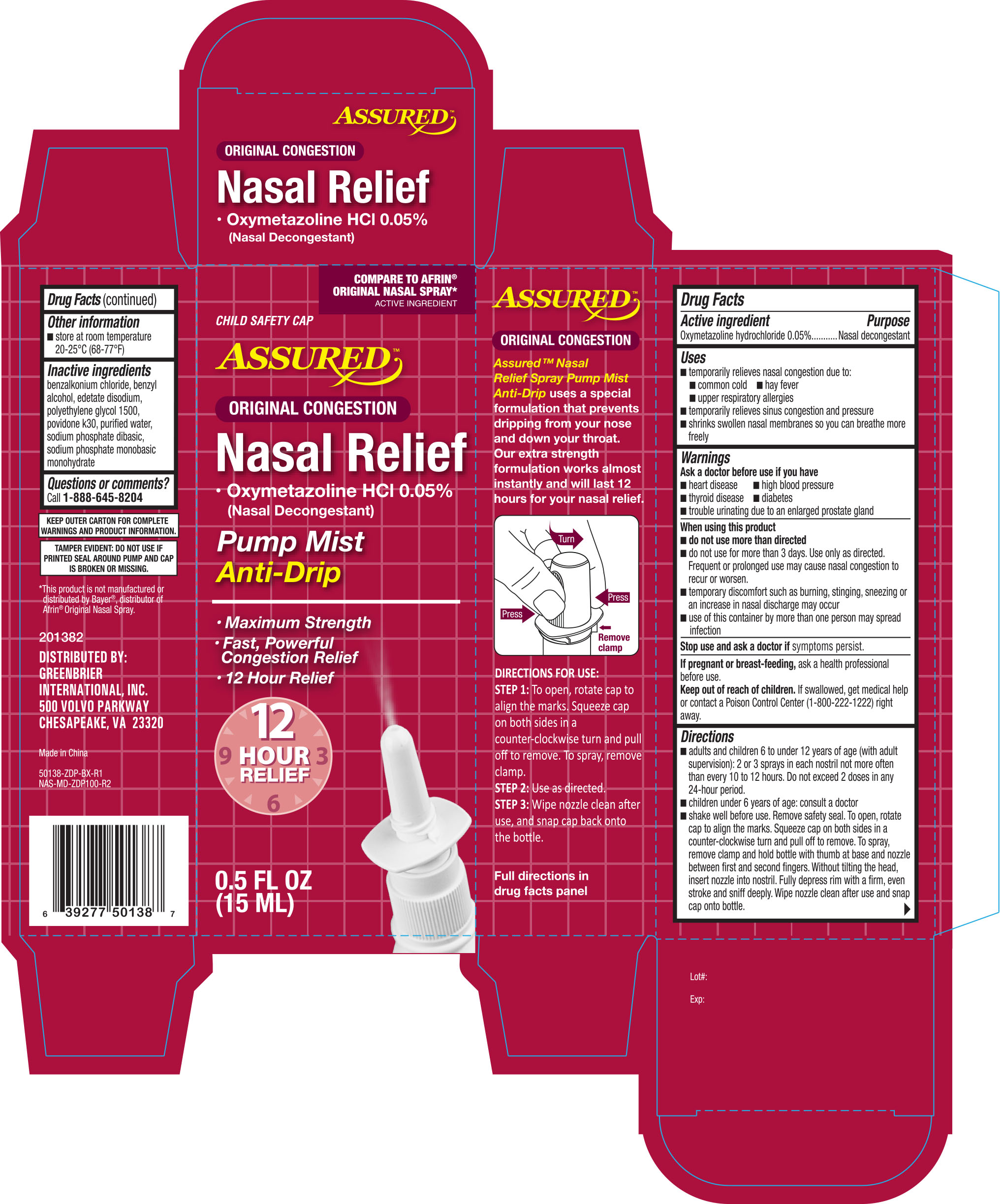 DRUG LABEL: ASSURED NASAL RELIEF ORIGINAL
NDC: 33992-8684 | Form: SPRAY
Manufacturer: GREENBRIER INTERNATIONAL, INC.
Category: otc | Type: HUMAN OTC DRUG LABEL
Date: 20220331

ACTIVE INGREDIENTS: OXYMETAZOLINE HYDROCHLORIDE 0.05 g/100 mL
INACTIVE INGREDIENTS: BENZALKONIUM CHLORIDE; BENZYL ALCOHOL; SODIUM PHOSPHATE, DIBASIC, DIHYDRATE; EDETATE DISODIUM; SODIUM PHOSPHATE, MONOBASIC, DIHYDRATE; POLYETHYLENE GLYCOL 1500; POVIDONE K30; WATER

Assured Nasal Spray Severe Congestion 0.5 oz (50138)

Active Ingredient Purpose

Oxymetazoline hydrochloride 0.05% ...........................................Nasal decongestant

Uses

- temporarily relieved nasal congestion due to:
- common cold
- hay fever
- upper respiratory allergies
- sinusitis
- shrinks swollen nasal membranes so you can breathe more freely

Warnings

For external use only

Ask a doctor before use if you have

- heart disease
- high blood pressure
- thyroid disease
- diabetes
- trouble urinating due to an enlarged prostate gland

When using this product

- do not use more than directed
- do not use more than 3 days. Use only as directed. Frequent or prolonged use may cause nasal congestion to recur or worsen
- temporary discomfort such as burning, stinging, sneezing or an increase in nasal discharge may occur
- use of this container by more than one person may spread infection

Stop use and ask a doctor if symptoms persist

PREGNANCY OR BREAST FEEDING

If pregnant or breast-feeding, ask a health professional before use.

Keep out of reach of children. If swallowed, get medical help or contact a Poison Control Center right away.

Directions

- adults and children 6 to 12 years of age (with adult supervision): 2 or 3 sprays in each nostril not more often than every 10 to 12 hours. Do not exceed 2 doses in any 24-hour period.
- children under 6 years of age: ask a doctor. To open, rotate cap to align the marks. Squeeze cap on both sides in a counter-clockwise turn and pull off to remove. To srapy, remove clamp and hold bottle with thumb at base and nozzle between first and second fingers. Without tiliting the head, insert nozzle into nostril. Fully depress rim with a firm, even stroke and sniff deeply. Wipe nozzle clean after use and snap cap back onto the bottle.

Other information

- store between 20o and 25oC (68o and 77oF)
- retain carton for future reference on full labeling

Inactive ingredients

benzalkonium chloride, benzyl alcohol, dibasic sodium phosphate hydrate, disodium EDTA, distilled water, monobasic sodium phosphate dihydrtate, PEG 1450, PVP K30

DOSAGE AND ADMINISTRATION

Distributed by:

Greenbrier International, Inc.

500 Volvo Parkway

Chesapeake, VA 23320

Made in Korea